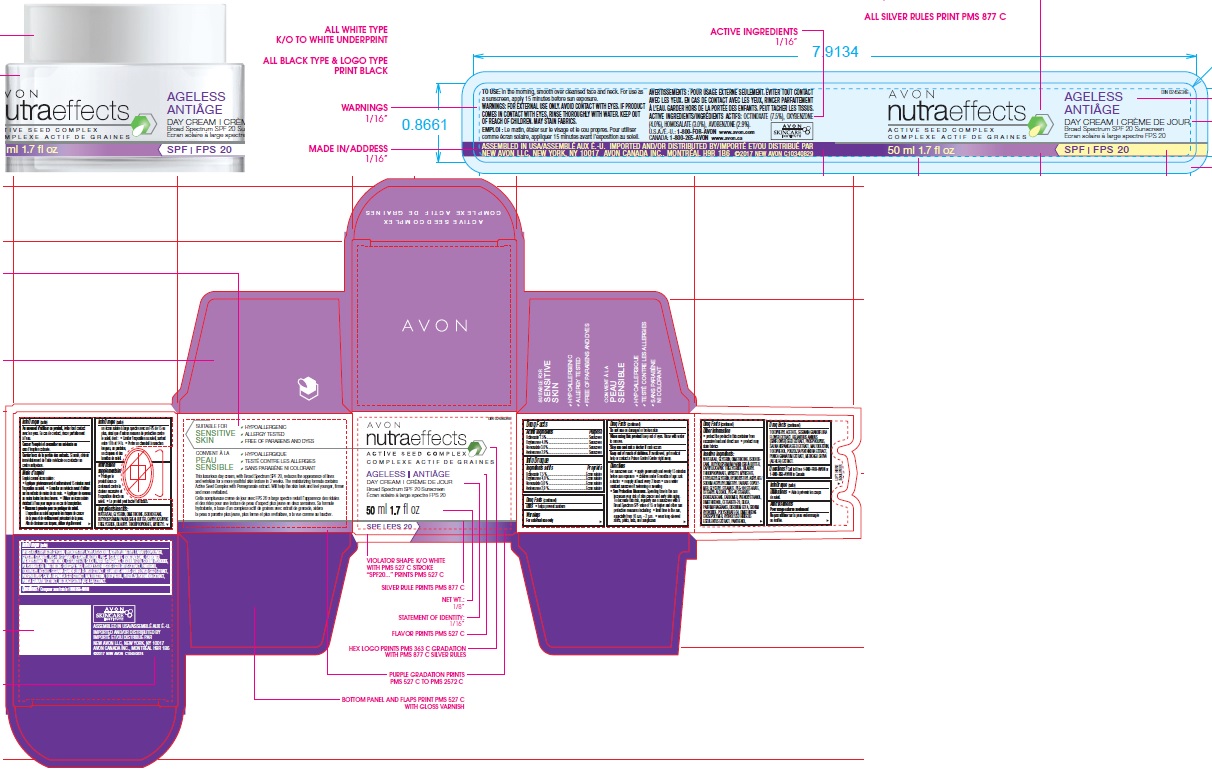 DRUG LABEL: Nutra Effects Ageless Day Cream SPF20
NDC: 10096-9501 | Form: CREAM
Manufacturer: New Avon LLC
Category: otc | Type: HUMAN OTC DRUG LABEL
Date: 20180402

ACTIVE INGREDIENTS: OCTINOXATE 7.5 g/100 g; OXYBENZONE 4 g/100 g; HOMOSALATE 3 g/100 g; AVOBENZONE 2.9 g/100 g
INACTIVE INGREDIENTS: WATER

Nutra Effects Ageless Day Cream SPF20

ACTIVE INGREDIENT

Active Ingredients/Ingrédients actifs:

OCTINOXATE (7.5 %), OXYBENZONE (4.0 %), HOMOSALATE (3.0 %), AVOBENZONE (2.9 %).

INDICATIONS & USAGE

Uses

- helps prevent sunburn

WARNINGS

For external use only

Do not use on damaged or broken skin

When using this product keep out of eyes. Rinse with water to remove.

Stop use and ask a doctor if rash occurs

Keep out of reach of children. If swallowed, get medical help or contact a Poison Control Center right away.

DOSAGE & ADMINISTRATION

Directions

- For sunscreen use:
- apply generously and evenly 15 minutes before sun exposure
- children under 6 months of age: ask a doctor
- reapply at least every 2 hours
- use a water resistant sunscreen if swimming or sweating

Sun Protection Measures. Spending time in the sun increases your risk of skin cancer and early skin aging. To decrease this risk, regularly use a sunscreen with a Broad Spectrum SPF value of 15 or higher and other sun protection measures including:

- limit time in the sun, especially from 10 a.m. – 2 p.m.
- wear long-sleeved shirts, pants, hats, and sunglasses

Other Information

- protect the product in this container from excessive heat and direct sun
- product may stain fabrics

INACTIVE INGREDIENT

Inactive Ingredients/Ingrédients inactifs: WATER/EAU, GLYCERIN, DIMETHICONE, ISODODECANE, BUTYROSPERMUM PARKII (SHEA) BUTTER, CAPRYLIC/CAPRIC TRIGLYCERIDE, DILAURYL THIODIPROPIONATE, MYRISTYL MYRISTATE, ETHYLHEXYLGLYCERIN, HYDROXYETHYL ACRYLATE/SODIUM ACRYLOYLDIMETHYL TAURATE COPOLYMER, GLYCERYL STEARATE, PEG-100 STEARATE, CETEARYL ALCOHOL, PEG-40 STEARATE, ISOHEXADECANE, CARBOMER, PHENOXYETHANOL, DIMETHICONOL, CETEARETH-20, SILICA, PARFUM/FRAGRANCE, DISODIUM EDTA, SODIUM HYDROXIDE, POLYSORBATE 60, DIMETHICONE CROSSPOLYMER, HYDROLYZED HIBISCUS ESCULENTUS EXTRACT, PANTHENOL, TOCOPHERYL ACETATE, SESBANIA GRANDIFLORA FLOWER EXTRACT, HELIANTHUS ANNUUS (SUNFLOWER) SEED EXTRACT, PHOSPHOLIPIDS, SALVIA HISPANICA SEED EXTRACT, MALTODEXTRIN, TOCOPHEROL, POUZOLZIA PENTANDRA EXTRACT, PUNICA GRANATUM EXTRACT, MEDICAGO SATIVA (ALFALFA) EXTRACT.

QUESTIONS

Questions or Comments?
Call toll free 1-800-FOR-AVON or 1-800-265-AVON in Canada